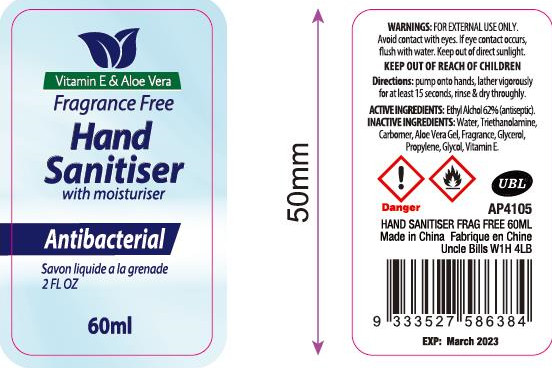 DRUG LABEL: hand sanitizer
NDC: 52989-001 | Form: LIQUID
Manufacturer: Taizhou Yadai Daily-Use Co., Ltd.
Category: otc | Type: HUMAN OTC DRUG LABEL
Date: 20200414

ACTIVE INGREDIENTS: ALCOHOL 37.2 mL/60 mL
INACTIVE INGREDIENTS: WATER

DOSAGE AND ADMINISTRATION

Keep out of direct sunligh

INACTIVE INGREDIENT

water

WARNINGS

FOR EXTERNAL USEONLY. Avoid contatwitheyes. If eye contact occours,fush with water. Keep out of direct sunlight

INDICATIONS AND USAGE

purmp onto hands, lteregrously for atleast 15second, rise and dry throughly

ACTIVE INGREDIENT

ethyl alcohol

keep out of children

PURPOSE

Disinfection
Sterilization